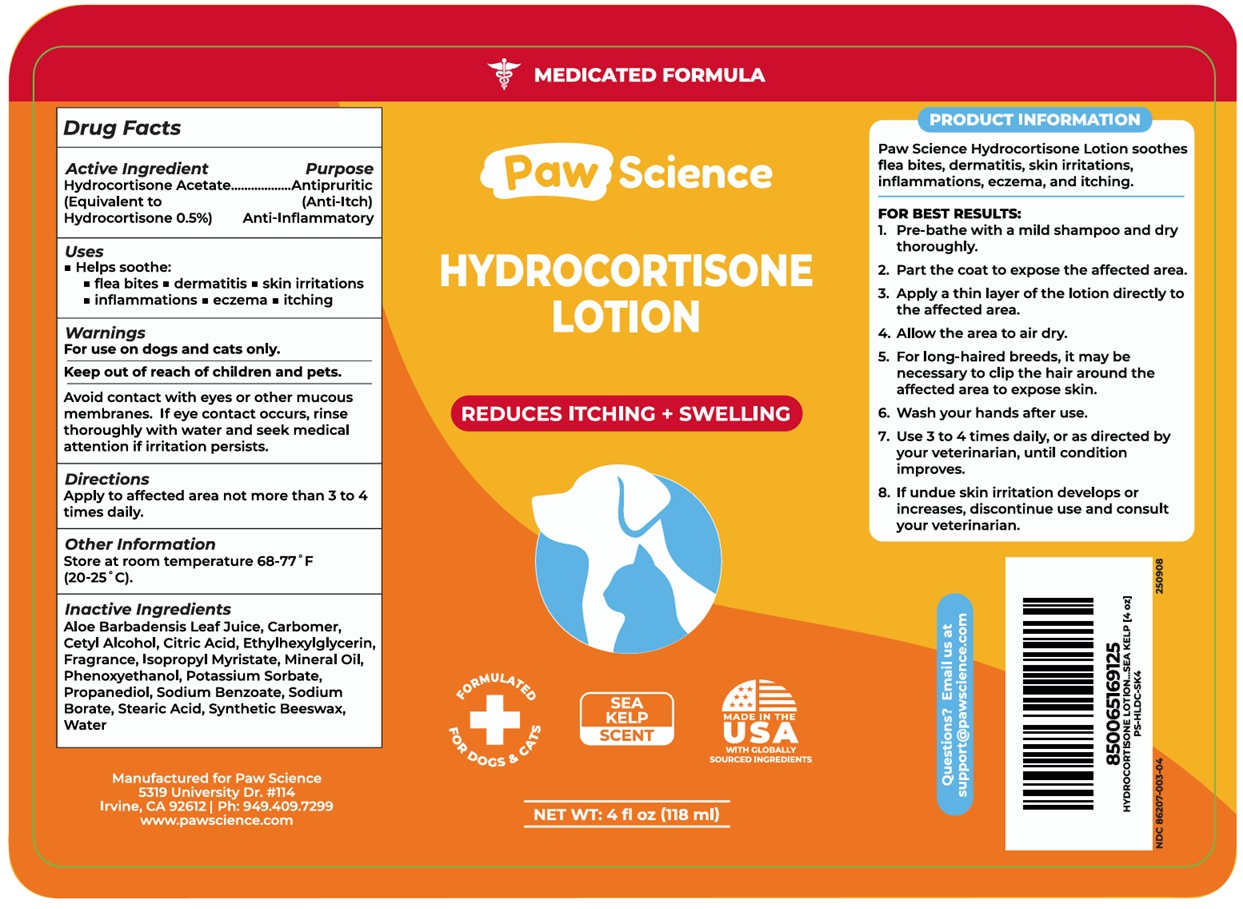 DRUG LABEL: Paw Science HYDROCORTISONE
NDC: 86207-003 | Form: LOTION
Manufacturer: Pet Science LLC
Category: animal | Type: OTC ANIMAL DRUG LABEL
Date: 20250827

ACTIVE INGREDIENTS: HYDROCORTISONE ACETATE 0.5 g/100 mL
INACTIVE INGREDIENTS: ALOE VERA LEAF JUICE; CARBOMER HOMOPOLYMER, UNSPECIFIED TYPE; CETYL ALCOHOL; CITRIC ACID MONOHYDRATE; ETHYLHEXYLGLYCERIN; ISOPROPYL MYRISTATE; MINERAL OIL; PHENOXYETHANOL; POTASSIUM SORBATE; PROPANEDIOL; SODIUM BENZOATE; SODIUM BORATE; STEARIC ACID; SYNTHETIC BEESWAX; WATER

Paw Science HYDROCORTISONE LOTION

Active Ingredient

Hydrocortisone Acetate
(Equivalent to Hydrocortisone 0.5%)

Purpose

Antipruritic (Anti-Itch)
Anti-Inflammatory

Uses

• Helps soothe:
• flea bites • dermatitis • skin irritations • inflammations • eczema • itching

Warnings

For use on dogs and cats only.

Keep out of reach of children and pets.
Avoid contact with eyes or other mucous membranes. If eye contact occurs, rinse thoroughly with water and seek medical attention if irritation persists.

Directions

• Apply to affected area not more than 3 to 4 times daily.

Other Information

• Store at room temperature 68-77°F (20-25°C).

Inactive Ingredients

Aloe Barbadensis Leaf Juice, Carbomer, Cetyl Alcohol, Citric Acid, Ethylhexylglycerin, Fragrance, Isopropyl Myristate, Mineral Oil, Phenoxyethanol, Potassium Sorbate, Propanediol, Sodium Benzoate, Sodium Borate, Stearic Acid, Synthetic Beeswax, Water

MEDICATED FORMULA

REDUCES ITCHING + SWELLING

FORMULATED FOR DOGS & CATS

SEA KELP SCENT

MADE IN THE USA WITH GLOBALLY SOURCED INGREDIENTS

PRODUCT INFORMATION

Paw Science Hydrocortisone Lotion soothes flea bites, dermatitis, skin irritations, inflammations, eczema, and itching.

FOR BEST RESULTS:
1. Pre-bathe with a mild shampoo and dry thoroughly.
2. Part the coat to expose the affected area.
3. Apply a thin layer of the lotion directly to the affected area.
4. Allow the area to air dry.
5. For long-haired breeds, it may be necessary to clip the hair around the affected area to expose skin.
6. Wash your hands after use.
7. Use 3 to 4 times daily, or as directed by your veterinarian, until condition improves.
8. If undue skin irritation develops or increases, discontinue use and consult your veterinarian.

Questions? Email us at support@pawscience.com

Manufactured for Paw Science
5319 University Dr. #114
Irvine, CA 92612 | Ph: 949.409.7299
www.pawscience.com